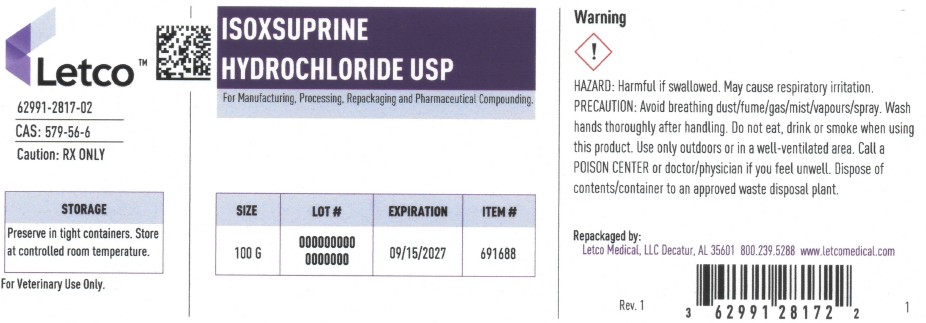 DRUG LABEL: ISOXSUPRINE HCL
NDC: 62991-2817 | Form: POWDER
Manufacturer: LETCO MEDICAL, LLC
Category: other | Type: BULK INGREDIENT - ANIMAL DRUG
Date: 20250926

ACTIVE INGREDIENTS: ISOXSUPRINE HYDROCHLORIDE 1 g/1 g

ISOXSUPRINE HCL USP

PACKAGE LABEL

Isoxsuprine Hydrochloride USP 100g